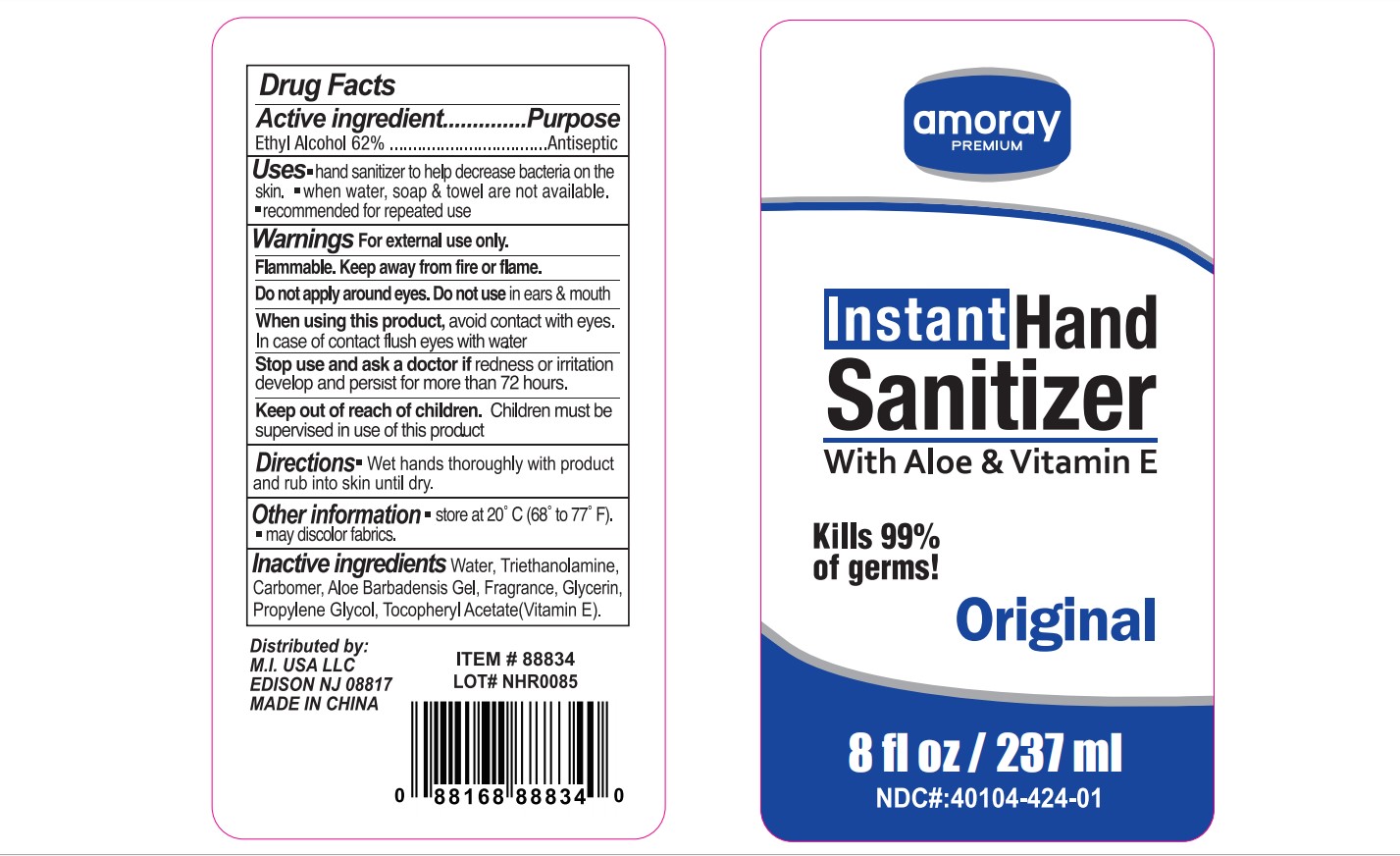 DRUG LABEL: Amoray Premium Instant Hand Sanitizer With Aloe and Vitamin E Original
NDC: 76114-005 | Form: SOLUTION
Manufacturer: Zhejiang Aidi Cosmetics Co., Ltd
Category: otc | Type: HUMAN OTC DRUG LABEL
Date: 20200424

ACTIVE INGREDIENTS: ALCOHOL 62 mL/100 mL
INACTIVE INGREDIENTS: GLYCERIN; WATER; CARBOMER 934; TRIETHANOLAMINE SULFATE; ALOE VERA WHOLE; PROPYLENE GLYCOL; .ALPHA.-TOCOPHEROL ACETATE

NA

Active Ingredient(s)

Ethyl Alcohol 62% v/v

Purpose

Antiseptic

Use

Hand sanitizer to help reduce bacteria on the skin

When water, soap, and towel are not available

Recommended for repeaded use

Warnings

For external use only.

Flammable. Keep away from fire or flame

WHEN USING

Do not apply around eyes

Do not use in ears and mouth

When using this product avoid contact with eyes. In case of contact, flush eyes with water.

Stop use and ask a doctor if redness or irritation develops and persists for more than 72 hours

Keep out of reach of children. Children must be supervised in use of this product.

Directions

Wet hands thoroughly with products and rub into skin until dry

Other information

Store at 20C (68-77F)

May discolor fabrics

Inactive ingredients

Water, triethanolamine, carbomer, aloe barbadensis gel, fragrance, glycerin, propylene glycol, tocopheryl acetate (Vitamin E)